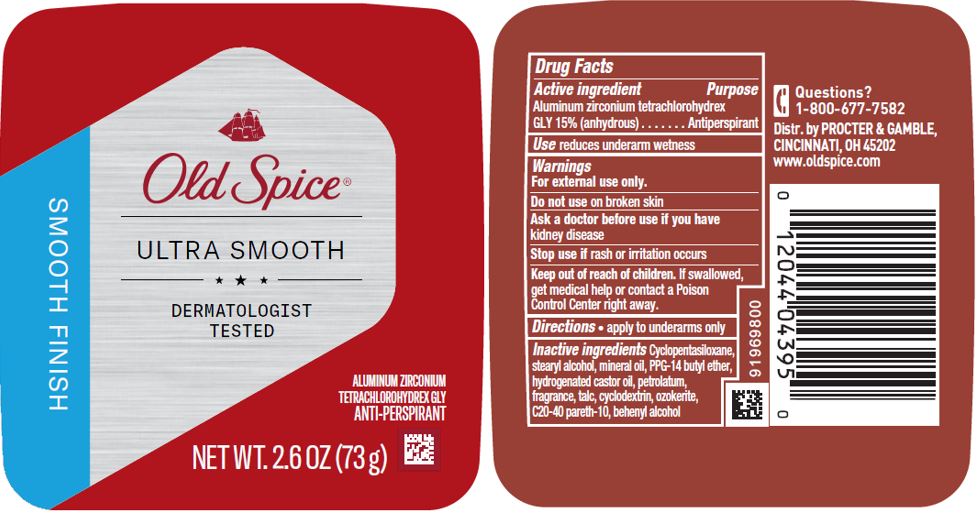 DRUG LABEL: Old Spice Ultra Smooth Smooth Finish
NDC: 69423-404 | Form: STICK
Manufacturer: The Procter & Gamble Manufacturing Company
Category: otc | Type: HUMAN OTC DRUG LABEL
Date: 20200330

ACTIVE INGREDIENTS: ALUMINUM ZIRCONIUM TETRACHLOROHYDREX GLY 15 g/100 g
INACTIVE INGREDIENTS: CYCLOMETHICONE 5; STEARYL ALCOHOL; PPG-14 BUTYL ETHER; HYDROGENATED CASTOR OIL; PETROLATUM; TALC; MINERAL OIL; DOCOSANOL; BETADEX; CERESIN; C20-40 PARETH-10

Old Spice Ultra Smooth Smooth Finish IS

Drug Facts

Active ingredient

Aluminum zirconium tetrachlorohydrex Gly 15% (anhydrous)

Purpose

Antiperspirant

Use

reduces underarm wetness

Warnings

For external use only.

Do not use on broken skin

Ask a doctor before use if you have kidney disease

Stop use if rash or irritation occurs

Keep out of reach of children. If swallowed, get medical help or contact a Poison Control Center right away.

Directions

- apply to underarms only

Inactive ingredients

Cyclopentasiloxane, stearyl alcohol, mineral oil, PPG-14 butyl ether, hydrogenated castor oil, petrolatum, fragrance, talc, cyclodextrin, ozokerite, C20-40 pareth-10, behenyl alcohol

Questions?

1-800-677-7582

Dist. by PROCTER & GAMBLE,
CINCINNATI, OH 45202.

PRINCIPAL DISPLAY PANEL 73 g Canister Label

Old Spice

ULTRA SMOOTH

SMOOTH FINISH

ALUMINUM ZIRCONIUM TETRACHLOROHYDREX GLY

ANTI-PERSPIRANT

NET WT. 2.6 OZ (73g)